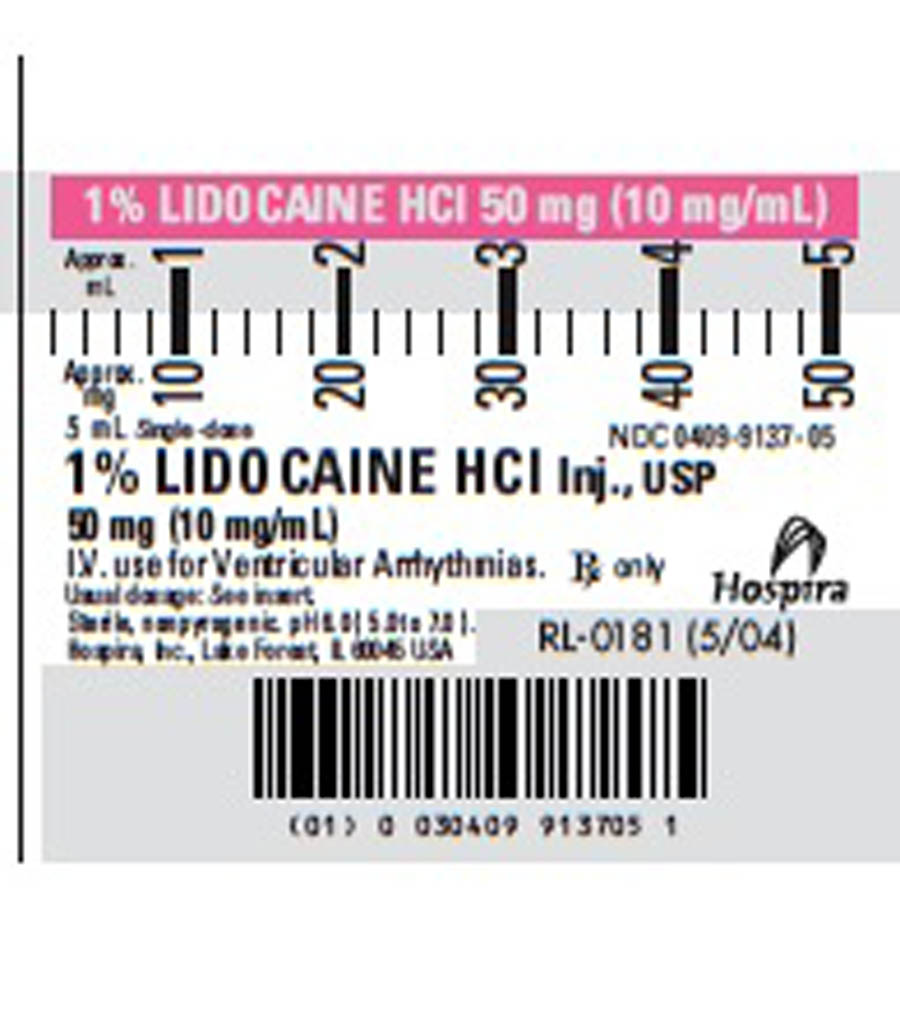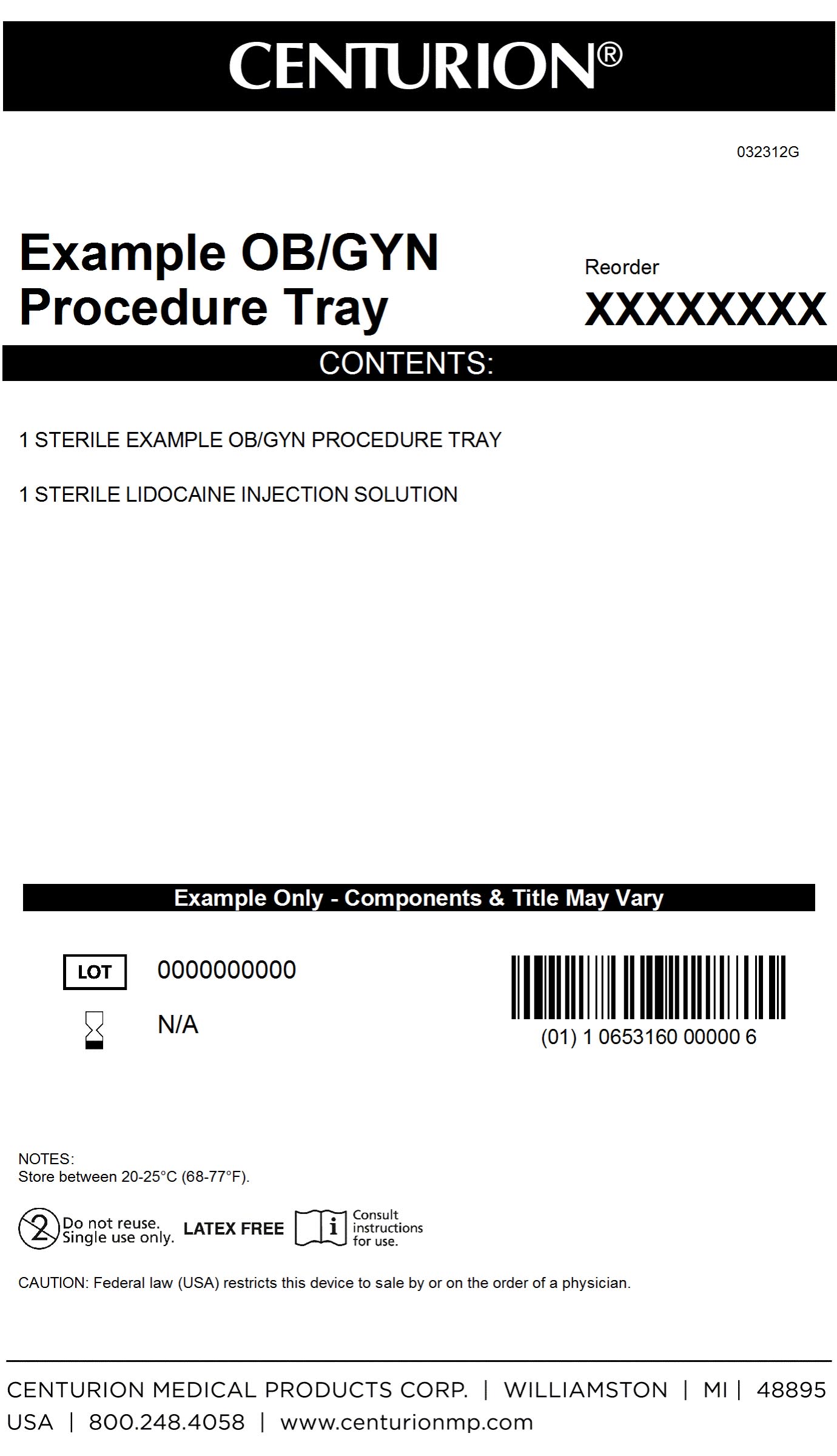 DRUG LABEL: OBGYN Procedure Kit
NDC: 24840-1705 | Form: KIT | Route: INTRAVENOUS
Manufacturer: Centurion Medical Products
Category: other | Type: MEDICAL DEVICE
Date: 20120531

ACTIVE INGREDIENTS: LIDOCAINE HYDROCHLORIDE 10 mg/1 mL
INACTIVE INGREDIENTS: SODIUM HYDROXIDE; HYDROCHLORIC ACID; SODIUM CHLORIDE

OBGYN Procedure Kit

DESCRIPTION

Lidocaine Hydrochloride Injection, USP is a sterile, nonpyrogenic solution of an antriarrhythmic agent administered interavenously by either direct injection or continuous infusion. It is available in the following concentration: 5mL (100 mg), 6.0 (5.0 to 7.0) pH. May contain sodium hydroxide and/or hydrocholoric acid for pH adjustment. Injections containing 10 mg/mL (1%) contain sodium chloride 7 mg and injections containing 20 mg/mL (2%) lidocaine hydrochloride contain sodium chloride 6 mg to adjust tonicity. Single dose solutions contain no preservative and unused portions must be discarded after use. Lidocaine Hydrochloride, USP is a white powder freely soluable in water. The molecular weight is 288.82. The plastic syringe is molded from a specially formulated polypropylene. Water permeates from inside the container at an extremely slow rate which will have an insignificant effect on solution concentration over the expected shelf life. Solutions in contact with the plastic container may leach out certain chemical components from the plastic in very small amounts; however, biological testing was supportive of the safety of the syringe material.

OBGYN Procedure Kit Primary Label

MM1

Lidocaine Label

MM1